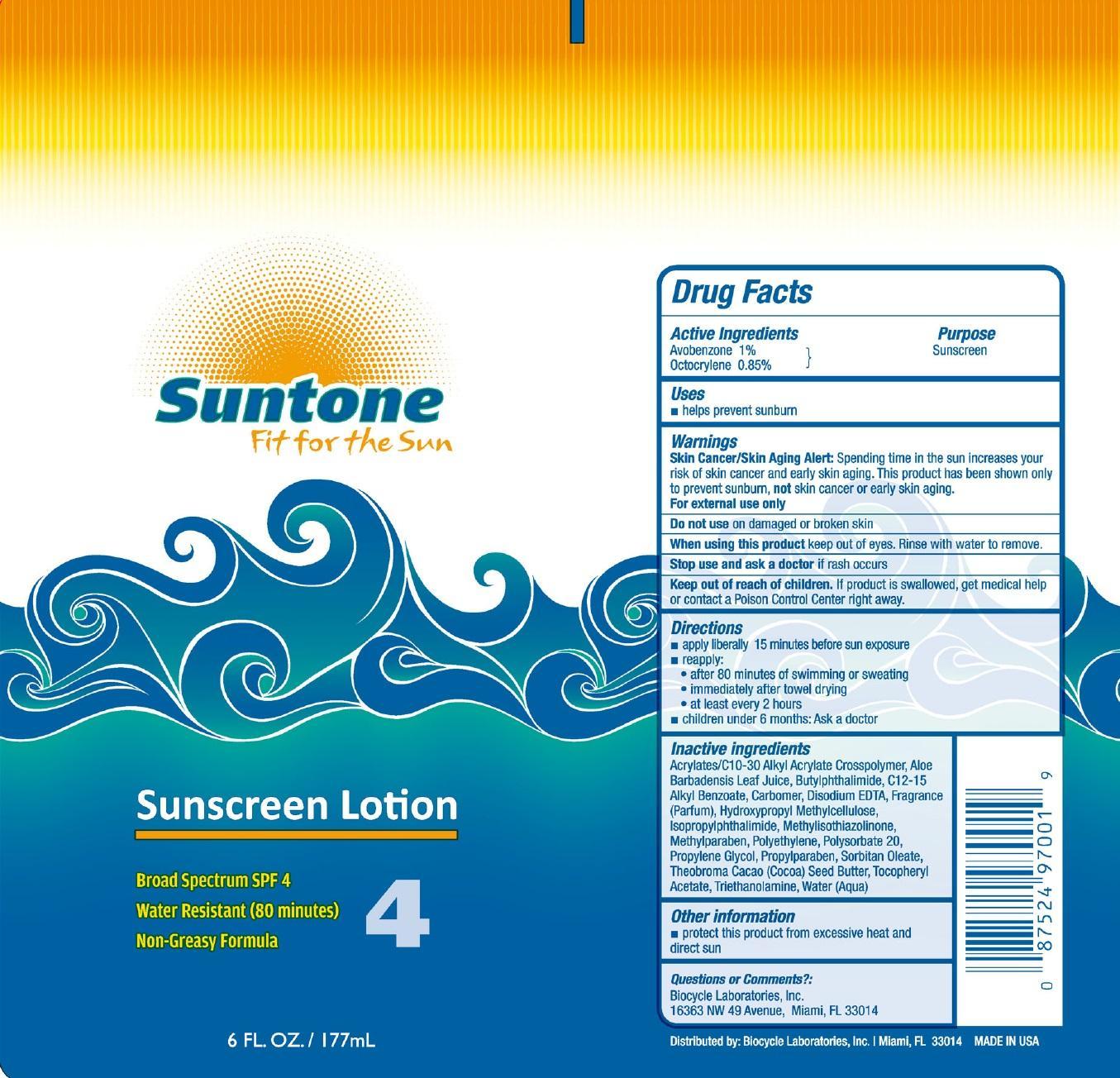 DRUG LABEL: Suntone
NDC: 58443-0100 | Form: LOTION
Manufacturer: Prime Enterprises, Inc.
Category: otc | Type: HUMAN OTC DRUG LABEL
Date: 20200117

ACTIVE INGREDIENTS: AVOBENZONE 9.9 mg/1 mL; OCTOCRYLENE 8.4 mg/1 mL
INACTIVE INGREDIENTS: CARBOMER COPOLYMER TYPE B (ALLYL PENTAERYTHRITOL CROSSLINKED); ALOE VERA LEAF; 3-BUTYLPHTHALIDE; ISOPROPYLPHTHALIMIDE; ALKYL (C12-15) BENZOATE; CARBOMER HOMOPOLYMER TYPE C (ALLYL PENTAERYTHRITOL CROSSLINKED); EDETATE DISODIUM; METHYLISOTHIAZOLINONE; METHYLPARABEN; HYPROMELLOSES; POLYSORBATE 20; HIGH DENSITY POLYETHYLENE; PROPYLENE GLYCOL; PROPYLPARABEN; SORBITAN MONOOLEATE; .ALPHA.-TOCOPHEROL ACETATE; TROLAMINE; WATER

Active ingredients

Avobenzone 1 %, Octocrylene 0.85 %

Purpose

Sunscreen

Uses

- helps prevent sunburn

Warnings

Skin Cancer/Skin Aging Alert: Spending time in the sun increases your risk of skin cancer and early skin aging. This product has been shown only to prevent sunburn, not skin cancer or early skin aging.

OTHER SAFETY INFORMATION

For external use only

Do not use on damaged or broken skin.

When using this product keep out of eyes. Rinse with water to remove.

Stop use and ask a doctor if rash occurs.

Keep out of reach of children. If product is swallowed, get medical help or contact a Poison Control Center right away.

Directions

- apply liberally 15 minutes before sun exposure
- reapply:
  - after 80 minutes of swimming or sweating
  - immediately after towel drying
  - at least every 2 hour
- children under 6 months: Ask a doctor

Inactive Ingredients

Acrylates/C10-30 Alkyl Acrylate Crosspolymer, Aloe Barbadensis Leaf Juice, Butylphthalimide, C12-15 Alkyl Benzoate, Carbomer, Disodium EDTA, Fragrance (Parfum), Hydroxypropyl Methylcellulose, Isopropylphthalimide, Methylisothiazolinone, Methylparaben, Polyethylene, Polysorbate 20, Propylene Glycol, Propylparaben, Sorbitan Oleate, Theobroma Cacao (Cocoa) Seed Butter, Tocopheryl Acetate, Triethanolamine, Water (Aqua)

Other information

- protect this product from excesive heat and direct sun

Questions or Comments?

Biocycle Laboratories, Inc.

16363 NW 49 Avenue, Miami, FL 33014

PRINCIPAL DISPLAY PANEL - 177 mL Can Label

Suntone

Fit for the sun

Sunscreen Lotion

Broad Spectrum SPF 4

Water Resistant (80 minutes)

Non-Greasy Formula

4

6 FL. OZ /177mL